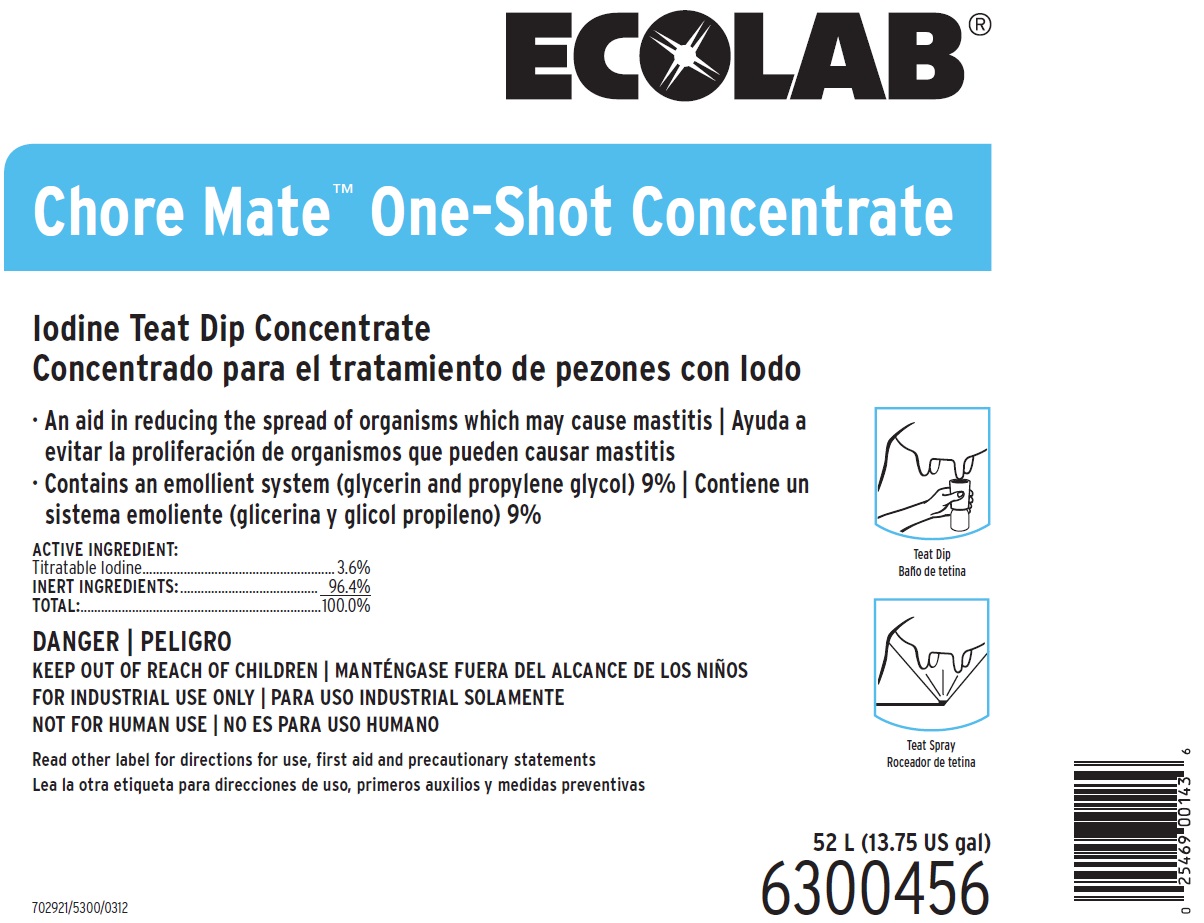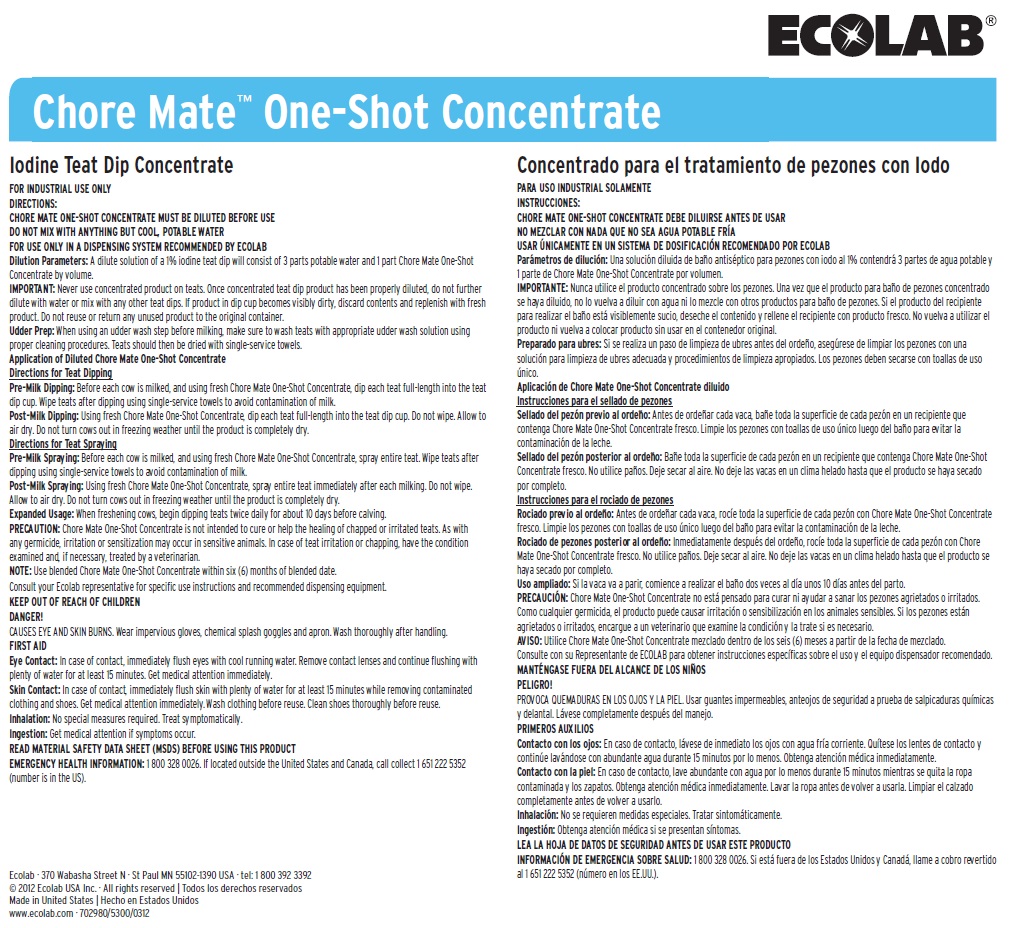 DRUG LABEL: Choremate One-Shot Concentrate
NDC: 47593-325 | Form: SOLUTION
Manufacturer: Ecolab Inc. 
Category: animal | Type: OTC ANIMAL DRUG LABEL
Date: 20250801

ACTIVE INGREDIENTS: IODINE 36 mg/1 mL
INACTIVE INGREDIENTS: WATER; GLYCERIN; PROPYLENE GLYCOL

SAFE HANDLING WARNING

DANGER

KEEP OUT OF REACH OF CHILDREN

FOR INDUSTRIAL USE ONLY

NOT FOR HUMAN USE

Read other label for directions for use, first aid and precautionary statements

CAUSES EYE AND SKIN BURNS. Wear impervious gloves, chemical splash goggles and apron. Wash thoroughly after handling.

DIRECTIONS:

CHORE MATE ONE-SHOT CONCENTRATE MUST BE DILUTED BEFORE USE

DO NOT MIX WITH ANYTHING BUT COOL, POTABLE WATER

FOR USE ONLY IN A DISPENSING SYSTEM RECOMMENDED BY ECOLAB

Dilution Parameters: A dilute solution of a 1% iodine teat dip will consist of 3 parts potable water and 1 part Chore Mate One-Shot Concentrate by volume.

IMPORTANT: Never use concentrated product on teats. Once concentrated teat dip product has been properly diluted, do not further dilute with water or mix with any other teat dips. If product in dip cup becomes visibly dirty, discard contents and replenish with fresh product. Do not reuse or return any unused product to the original container.

Udder Prep: When using an udder wash step before milking, make sure to wash teats with appropriate udder wash solution using proper cleaning procedures. Teats should then be dried with single-service towels.

Application of Diluted Chore Mate One-Shot Concentrate

Directions for Teat Dipping

Pre-Milk Dipping: Before each cow is milked, and using fresh Chore Mate One-Shot Concentrate, dip each teat full-length into the teat dip cup. Wipe teats after dipping using single-service towels to avoid contamination of milk.

Post-Milk Dipping: Using fresh Chore Mate One-Shot Concentrate, dip each teat full-length into the teat dip cup. Do not wipe. Allow to air dry. Do not turn cows out in freezing weather until the product is completely dry.

Directions for Teat Spraying

Pre-Milk Spraying: Before each cow is milked, and using fresh Chore Mate One-Shot Concentrate, spray entire teat. Wipe teats after dipping using single-service towels to avoid contamination of milk.

Post-Milk Spraying: Using fresh Chore Mate One-Shot Concentrate, spray entire teat immediately after each milking. Do not wipe. Allow to air dry. Do not turn cows out in freezing weather until the product is completely dry.

Expanded Usage: When freshening cows, begin dipping teats twice daily for about 10 days before calving.

PRECAUTION: Chore Mate One-Shot Concentrate is not intended to cure or help the healing of chapped or irritated teats. As with any germicide, irritation or sensitization may occur in sensitive animals. In case of teat irritation or chapping, have the condition examined and, if necessary, treated by a veterinarian.

NOTE: Use blended Chore Mate One-Shot Concentrate within six (6) months of blended date.

Consult your Ecolab representative for specific use instructions and recommended dispensing equipment.

OTHER SAFETY INFORMATION

FIRST AID

Eye Contact: In case of contact, immediately flush eyes with cool running water. Remove contact lenses and continue flushing with plenty of water for at least 15 minutes. Get medical attention immediately.

Skin Contact: In case of contact, immediately flush skin with plenty of water for at least 15 minutes while removing contaminated clothing and shoes. Get medical attention immediately. Wash clothing before reuse. Clean shoes thoroughly before reuse. Inhalation: No special measures required. Treat symptomatically.

Ingestion: Get medical attention if symptoms occur.

READ MATERIAL SAFETY DATA SHEET (MSDS) BEFORE USING THIS PRODUCT

EMERGENCY HEALTH INFORMATION: 1 800 328 0026. If located outside the United States and Canada, call collect 1 651 222 5352 (number is in the US).

Representative label & Principal Display Panel

ECOLAB

Chore Mate™ One-Shot Concentrate

Iodine Teat Dip Concentrate

- An aid in reducing the spread of organisms which may cause mastitis
- Contains an emollient system (glycerin and propylene glycol) 9%

ACTIVE INGREDIENT:

Titratable Iodine.........................................................3.6%

INERT INGREDIENTS:......................................... 96.4%

TOTAL:......................................................................100.0%

52 L (13.75 US gal)

6300456

Ecolab · 370 Wabasha Street N · St Paul MN 55102-1390 USA · tel: 1 800 392 3392

© 2012 Ecolab USA Inc. · All rights reserved

Made in United States

www.ecolab.com · 702980/5300/0312